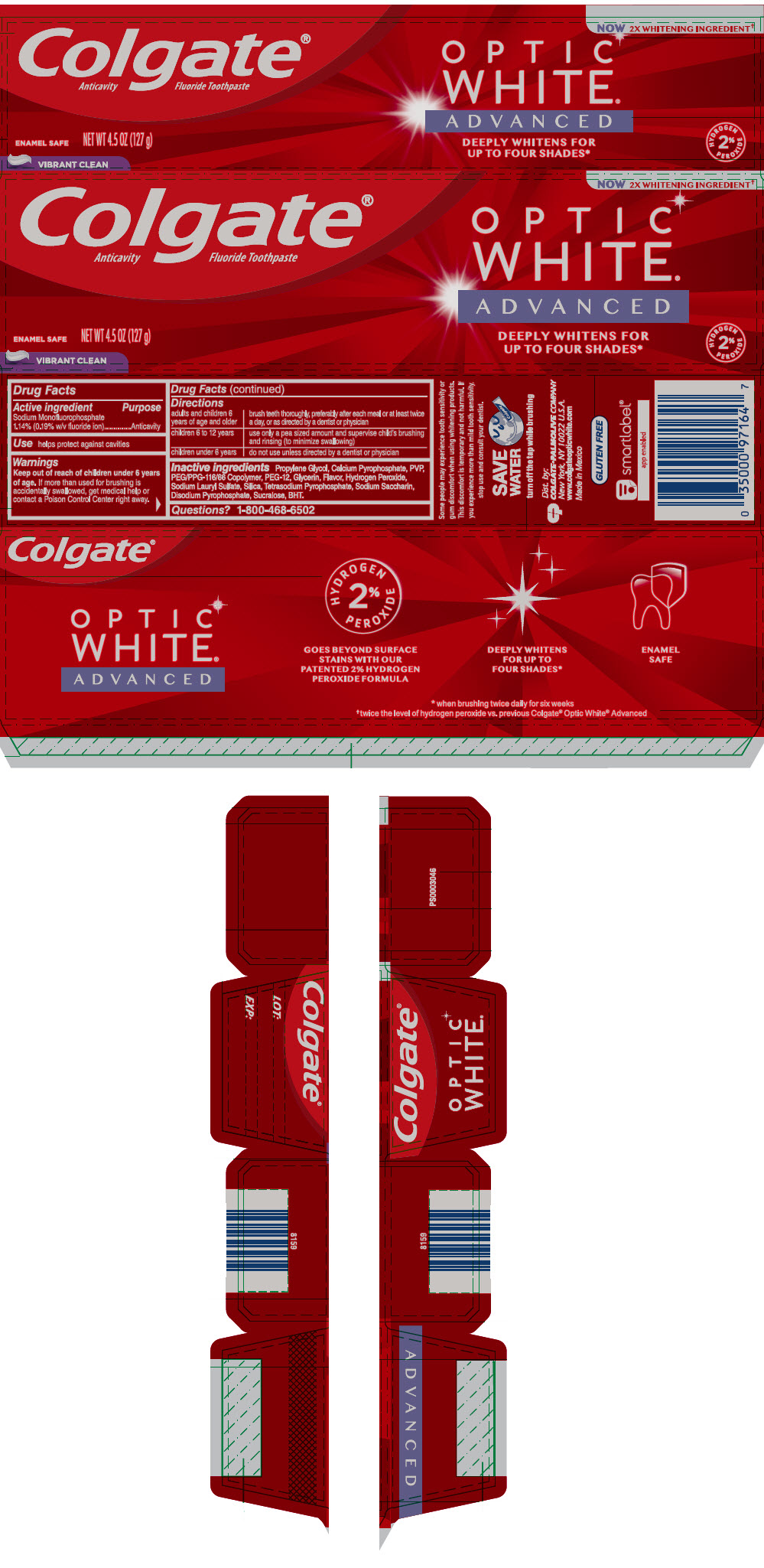 DRUG LABEL: COLGATE OPTIC WHITE ADVANCED VIBRANT CLEAN
NDC: 35000-979 | Form: PASTE, DENTIFRICE
Manufacturer: Colgate-Palmolive Company
Category: otc | Type: HUMAN OTC DRUG LABEL
Date: 20251021

ACTIVE INGREDIENTS: SODIUM MONOFLUOROPHOSPHATE 1.5 mg/1 g
INACTIVE INGREDIENTS: PROPYLENE GLYCOL 398 mg/1 g; CALCIUM PYROPHOSPHATE; POVIDONE K15; PEG/PPG-116/66 COPOLYMER; POLYETHYLENE GLYCOL 600; GLYCERIN; HYDROGEN PEROXIDE; SODIUM LAURYL SULFATE; SILICON DIOXIDE; SODIUM PYROPHOSPHATE; SACCHARIN SODIUM; SODIUM ACID PYROPHOSPHATE; SUCRALOSE; BUTYLATED HYDROXYTOLUENE

Colgate® Optic White® Advanced Vibrant Clean Toothpaste

Drug Facts

Active ingredient

Sodium Monofluorophosphate 1.14% (0.19% w/v fluoride ion)

Purpose

Anticavity

Use

helps protect against cavities

Warnings

Keep out of reach of children under 6 years of age. If more than used for brushing is accidentally swallowed, get medical help or contact a Poison Control Center right away.

Directions

adults and children 6 years of age and older | brush teeth thoroughly, preferably after each meal or at least twice a day, or as directed by a dentist or physician
children 6 to 12 years | use only a pea sized amount and supervise child's brushing and rinsing (to minimize swallowing)
children under 6 years | do not use unless directed by a dentist or physician

Inactive ingredients

Propylene Glycol, Calcium Pyrophosphate, PVP, PEG/PPG-116/66 Copolymer, PEG-12, Glycerin, Flavor, Hydrogen Peroxide, Sodium Lauryl Sulfate, Silica, Tetrasodium Pyrophosphate, Sodium Saccharin, Disodium Pyrophosphate, Sucralose, BHT.

Questions?

1-800-468-6502

Dist. by:
COLGATE-PALMOLIVE COMPANY
New York, NY 10022 U.S.A.

PRINCIPAL DISPLAY PANEL - 127 g Tube Carton

Colgate®
Anticavity Fluoride Toothpaste

NOW 2X WHITENING INGREDIENT†

OPTIC
WHITE®
ADVANCED

DEEPLY WHITENS FOR
UP TO FOUR SHADES*

HYDROGEN
2%
PEROXIDE

ENAMEL SAFE

NET WT 4.5 OZ (127 g)

VIBRANT CLEAN